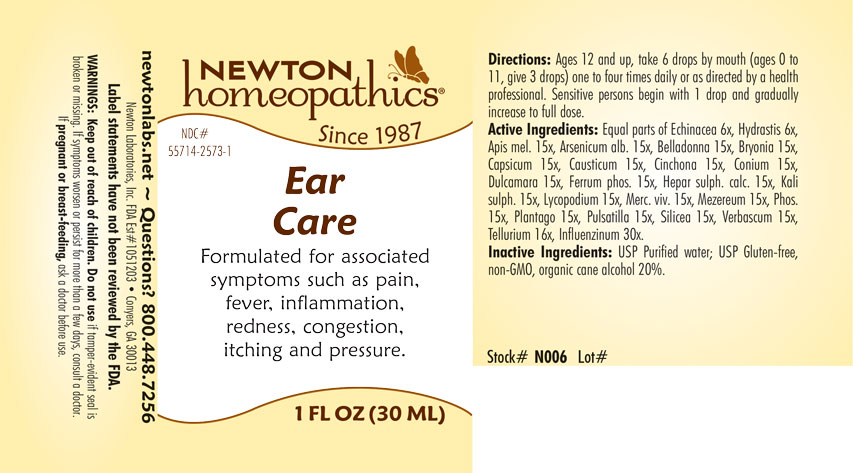 DRUG LABEL: Ear Care
NDC: 55714-2573 | Form: LIQUID
Manufacturer: Newton Laboratories, Inc.
Category: homeopathic | Type: HUMAN OTC DRUG LABEL
Date: 20220318

ACTIVE INGREDIENTS: INFLUENZA A VIRUS 30 [hp_X]/1 mL; TELLURIUM 16 [hp_X]/1 mL; APIS MELLIFERA 15 [hp_X]/1 mL; ARSENIC TRIOXIDE 15 [hp_X]/1 mL; ATROPA BELLADONNA 15 [hp_X]/1 mL; BRYONIA ALBA ROOT 15 [hp_X]/1 mL; CAPSICUM 15 [hp_X]/1 mL; CAUSTICUM 15 [hp_X]/1 mL; CINCHONA OFFICINALIS BARK 15 [hp_X]/1 mL; CONIUM MACULATUM FLOWERING TOP 15 [hp_X]/1 mL; SOLANUM DULCAMARA TOP 15 [hp_X]/1 mL; FERROSOFERRIC PHOSPHATE 15 [hp_X]/1 mL; CALCIUM SULFIDE 15 [hp_X]/1 mL; POTASSIUM SULFATE 15 [hp_X]/1 mL; LYCOPODIUM CLAVATUM SPORE 15 [hp_X]/1 mL; MERCURY 15 [hp_X]/1 mL; DAPHNE MEZEREUM BARK 15 [hp_X]/1 mL; PHOSPHORUS 15 [hp_X]/1 mL; PLANTAGO MAJOR 15 [hp_X]/1 mL; PULSATILLA VULGARIS 15 [hp_X]/1 mL; SILICON DIOXIDE 15 [hp_X]/1 mL; VERBASCUM THAPSUS 15 [hp_X]/1 mL; ECHINACEA, UNSPECIFIED 6 [hp_X]/1 mL; GOLDENSEAL 6 [hp_X]/1 mL; INFLUENZA B VIRUS 30 [hp_X]/1 mL
INACTIVE INGREDIENTS: ALCOHOL; WATER

EarCa 2573L

INDICATIONS & USAGE SECTION

Formulated for associated symptoms such as pain, fever, inflammation, redness, congestion, itching and pressure.

DOSAGE & ADMINISTRATION SECTION

Directions: Ages 12 and up, take 6 drops by mouth (ages 0 to 11, give 3 drops) one to four times daily or as directed by a health professional. Sensitive persons begin with 1 drop and gradually increase to full dose.

OTC - ACTIVE INGREDIENT SECTION

Equal parats of Echinacea 6x, Hydrastis 6x, Apis mel. 15x, Arsenicum alb. 15x, Belladonna 15x, Bryonia 15x, Capsicum 15x, Causticum 15x, Cinchona 15x, Conium 15x, Dulcamara 15x, Ferrum phos. 15x, Hepar sulph. calc. 15x, Kali sulph. 15x, Lycopodium 15x, Merc. viv. 15x, Mezereum 15x, Phos. 15x, Plantago 15x, Pulsatilla 15x, Silicea 15x, Verbascum 15x, Tellurium 16x, Influenzinum 30x.

OTC - PURPOSE SECTION

Formulated for associated symptoms such as pain, fever, inflammation, redness, congestion, itching and pressure.

INACTIVE INGREDIENT SECTION

Inactive Ingredients: USP Purified Water; USP Gluten-free, non-GMO, organic cane alcohol 20%.

QUESTIONS SECTION

newtonlabs.net - Questions? 800.448.7256

Newton Laboratories, Inc. FDA Est # 1051203 - Conyers, GA 30013

WARNINGS SECTION

WARNINGS: Keep out of reach of children. Do not use if tamper-evident seal is broken or missing. If symptoms worsen or persist for more than a few days, consult a doctor. If pregnant or breast-feeding, ask a doctor before use.

OTC - PREGNANCY OR BREAST FEEDING SECTION

If pregnant or breast-feeding, ask a doctor before use.

OTC - KEEP OUT OF REACH OF CHILDREN SECTION

Keep out of reach of children.